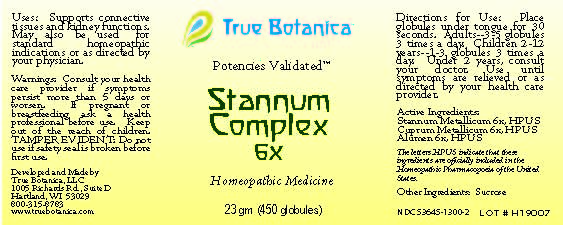 DRUG LABEL: Stannum Complex
NDC: 53645-1300 | Form: GLOBULE
Manufacturer: True Botanica, LLC
Category: homeopathic | Type: HUMAN OTC DRUG LABEL
Date: 20240506

ACTIVE INGREDIENTS: COPPER 6 [hp_X]/23 g; POTASSIUM ALUM 6 [hp_X]/23 g; TIN 6 [hp_X]/23 g
INACTIVE INGREDIENTS: SUCROSE

Stannum Complex 6X

ACTIVE INGREDIENT

Stannum Metallicum 6X, HPUS

Cuprum Metallicum 6X, HPUS

Alumen 6X, HPUS

The letters HPUS indicate that these ingredients are officially included in the Homeopathic Pharmacopoeia of the United States.

PURPOSE

Supports connective tissues and kidney functions. May also be used for standard homeopathic indications or as directed by your physician.

Use:

Supports connective tissues and kidney function. May also be used for standard homeopathic indications or as directed by your physician.

Warnings:

Consult your health care provider if symptoms persist more than 5 days or worsen.

PREGNANCY OR BREAST FEEDING

If pregnant or breastfeeding ask a health professional before use.

Keep out of the reach of children.

DO NOT USE

TAMPER EVIDENT: Do not use if safety seal is broken before first use.

Directions for Use:

Place globules under tongue for 30 seconds. Adults~3-5 globules 3 times a day. Children 2-12 years ~ 1-3 globules 3 times a day. Under 2 years, consult your doctor. Use until symptoms are relieved or as directed by your health care provider.

Other Ingredients:

Sucrose

QUESTIONS

Developed and Made by

True Botanica, LLC

1005 Richards Rd., Suite D

Hartland, WI 53029

800-315-8783

www.truebotanica.com